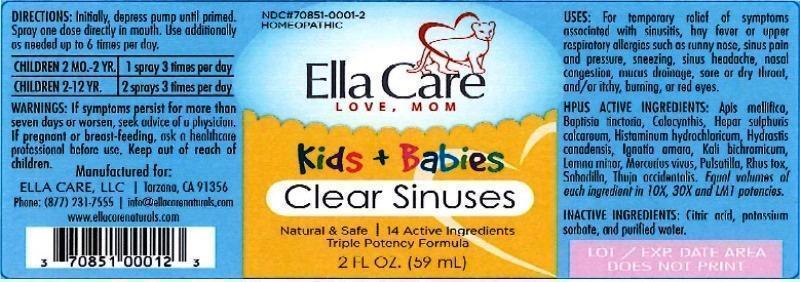 DRUG LABEL: Clear Sinuses
NDC: 70851-0001 | Form: LIQUID
Manufacturer: Ella Care, LLC
Category: homeopathic | Type: HUMAN OTC DRUG LABEL
Date: 20160901

ACTIVE INGREDIENTS: APIS MELLIFERA 10 [hp_X]/59 mL; BAPTISIA TINCTORIA ROOT 10 [hp_X]/59 mL; CITRULLUS COLOCYNTHIS FRUIT PULP 10 [hp_X]/59 mL; CALCIUM SULFIDE 10 [hp_X]/59 mL; HISTAMINE DIHYDROCHLORIDE 10 [hp_X]/59 mL; GOLDENSEAL 10 [hp_X]/59 mL; STRYCHNOS IGNATII SEED 10 [hp_X]/59 mL; POTASSIUM DICHROMATE 10 [hp_X]/59 mL; LEMNA MINOR 10 [hp_X]/59 mL; MERCURY 10 [hp_X]/59 mL; PULSATILLA VULGARIS 10 [hp_X]/59 mL; TOXICODENDRON PUBESCENS LEAF 10 [hp_X]/59 mL; SCHOENOCAULON OFFICINALE SEED 10 [hp_X]/59 mL; THUJA OCCIDENTALIS LEAFY TWIG 10 [hp_X]/59 mL
INACTIVE INGREDIENTS: ANHYDROUS CITRIC ACID; POTASSIUM SORBATE; WATER

Clear Sinuses

DOSAGE AND ADMINISTRATION

Directions: Initially depress pump until primed. Spray one dose directly in mouth. Use additionally as needed up to 6 times per day.

Children 2 MO-2YR: 1 spray 3 times per day

Children 2-12 YR: 2 spray 3 times per day

WARNINGS

Warnings: If symptoms persist more than seven days or worsen, seek advice of a physician. If pregnant or breast-feeding, ask a healthcare professional before use.

Keep out of reach of children.

PURPOSE

Indications: For temporary relief of symptoms associated with sinusitis, hay fever or upper respiratory allergies such as runny nose, sinus pain and pressure, sneezing, sinus headache, nasal congestion, mucus drainage, sore or dry throat, and / or itchy, burning, or red eyes.

ACTIVE INGREDIENT

Active Ingredients: Apis mellifica, Baptisia tinctoria, Colocynthis, Hepar sulphuris calcareum, Histaminum hydrochloricum, Hydrastis canadensis, Ignatia amara, Kali bichromicum, Lemna minor, Mercurius vivus, Pulsatilla, Rhus toxicodendron, Sabadilla, Thuja occidentalis. Equal volumes of each ingredient in 10X, 30X, and LM1 potencies.

Inactive Ingredient: Citric acid, potassium sorbate, and purified water.

INDICATIONS AND USAGE

Indications: For temporary relief of symptoms associated with sinusitis hay fever or upper respiratory allergies such as:

- runny nose
- sinus pain and pressure
- sneezing
- sinus headache
- nasal congestion
- mucus drainage
- sore or dry throat
- itchy, burning, or red eyes